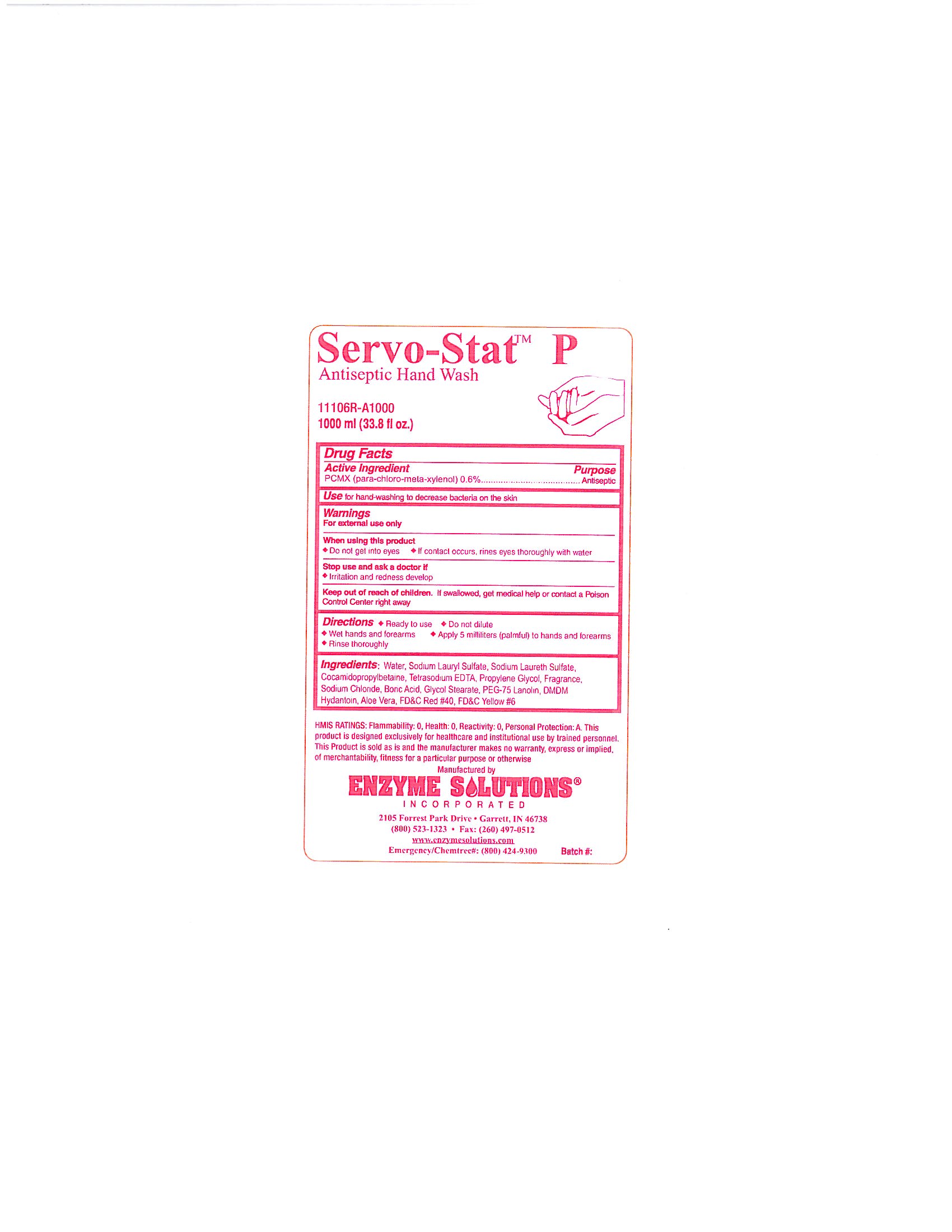 DRUG LABEL: Servo-Stat P
NDC: 76378-017 | Form: LIQUID
Manufacturer: Enzyme Solutions, Inc.
Category: otc | Type: HUMAN OTC DRUG LABEL
Date: 20241126

ACTIVE INGREDIENTS: CHLOROXYLENOL 0.6 g/100 mL
INACTIVE INGREDIENTS: WATER; SODIUM LAURETH SULFATE; COCAMIDOPROPYL BETAINE; EDETATE SODIUM; PROPYLENE GLYCOL; SODIUM CHLORIDE; BORIC ACID; GLYCOL STEARATE; PEG-75 LANOLIN; DMDM HYDANTOIN; ALOE VERA LEAF; FD&C RED NO. 40; FD&C YELLOW NO. 6; SODIUM LAURYL SULFATE

Drug Facts 76378-017

Active Ingredient

PCMX (para-chloro-meta-xylenol) 0.6%

Purpose

Antiseptic

Use

for hand-washing to decrease bacteria on the skin

Warnings

For external use only

When using this product

Do not get in eyes

If contact occurs, rinse eyes thoroughly with water

Stop use and ask a doctor if

Irritation and redness develop

Keep out of reach of children.

If swallowed, get medical help or contact a Poison Control Center right away

Directions

Ready to use

Do not dilute

Wet hands and forearms

Apply 5 milliliters (palmful) to hands and forearms

Rinse thoroughly

INACTIVE INGREDIENT

Ingredients

Water, Sodium Lauryl Sulfate, Sodium Laureth Sulfate, Cocamidopropylbetaine, Tetrasodium EDTA, Propylene Glycol, Fragrance, Sodium Chloride, Boric Acid, Glycol Stearate, PEG-75 Lanolin, DMDM Hydantoin, Aloe Vera, FDC Red #40, FDC Yellow #6

PACKAGE LABEL

Servo-Stat P

Antiseptic Hand Wash

11106R-A1000

1000 ml (33.8 fl oz.)